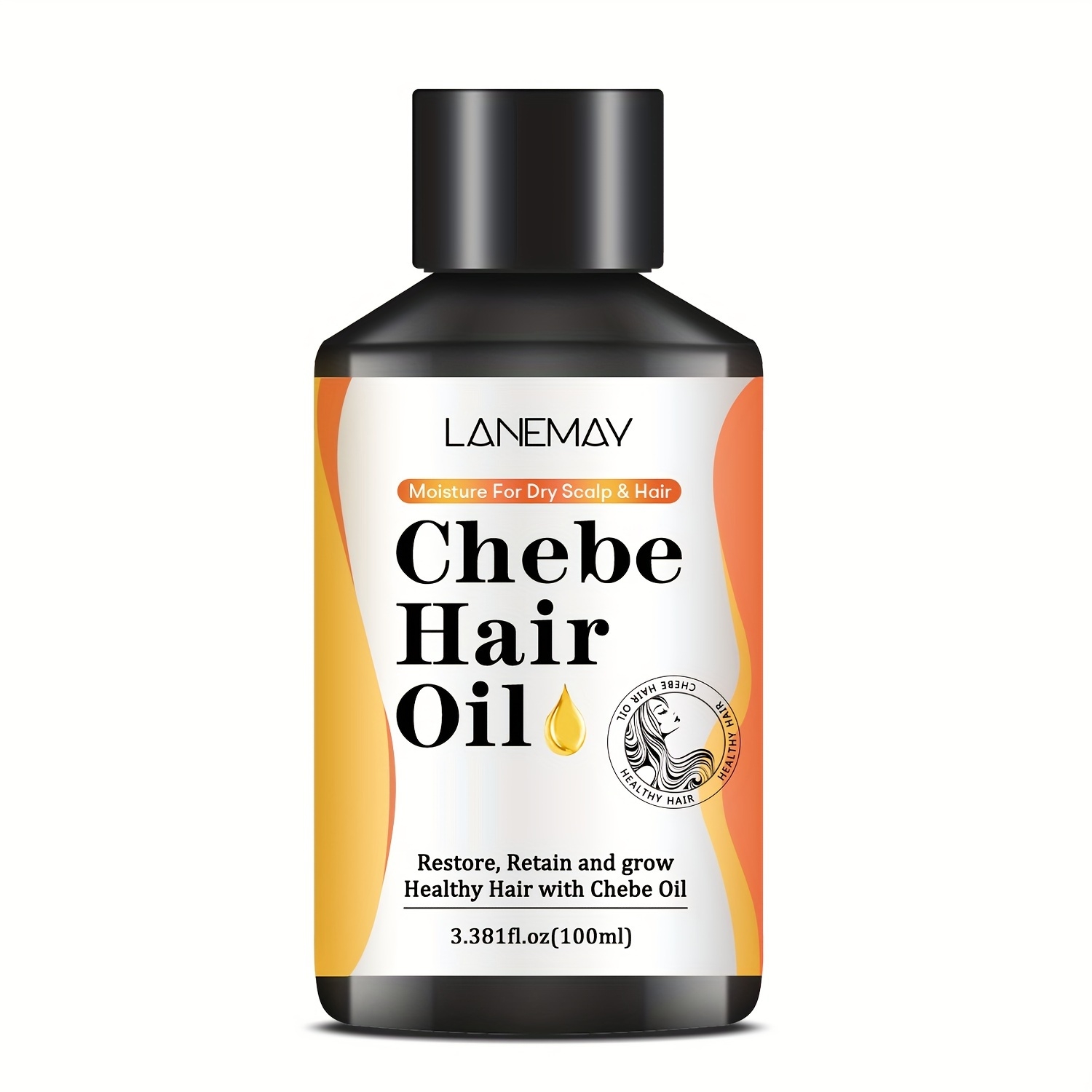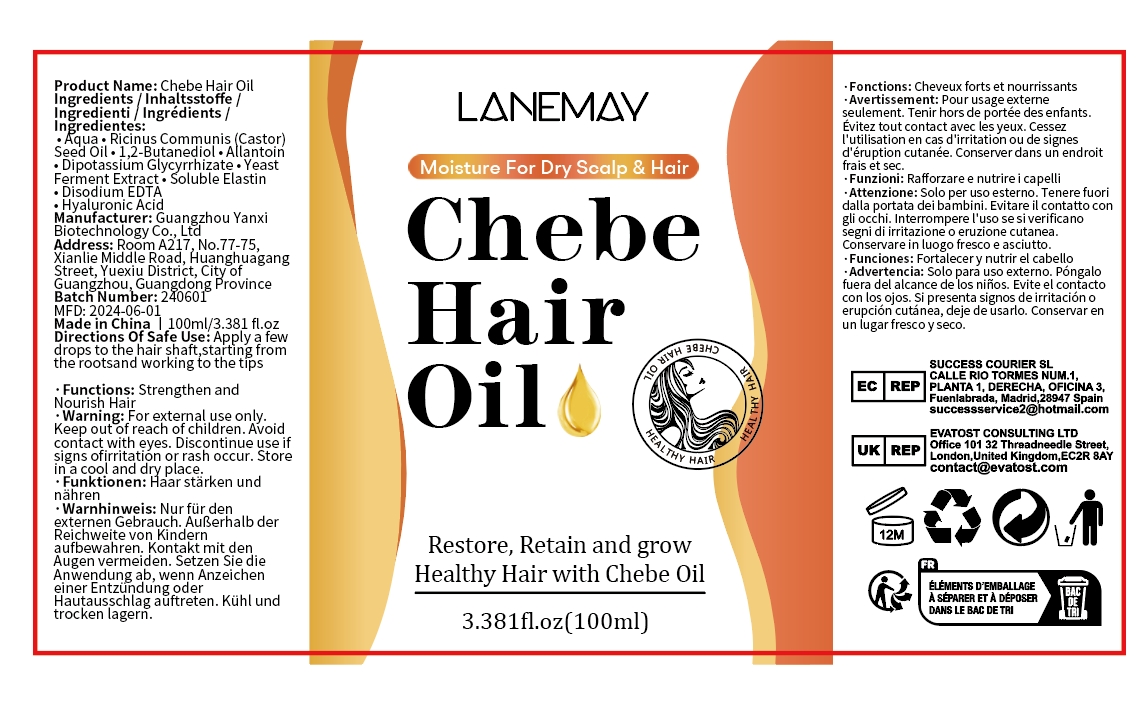 DRUG LABEL: Chebe Hair Oil
NDC: 84025-075 | Form: OIL
Manufacturer: Guangzhou Yanxi Biotechnology Co.. Ltd
Category: otc | Type: HUMAN OTC DRUG LABEL
Date: 20240720

ACTIVE INGREDIENTS: 1,2-BUTANEDIOL 5 mg/100 mL; ALLANTOIN 3 mg/100 mL
INACTIVE INGREDIENTS: WATER

DOSAGE AND ADMINISTRATION

Nourishes scalp

WARNINGS

keep out of children

INACTIVE INGREDIENT

Aqua

INDICATIONS AND USAGE

Treats dry hair and hair fall

keep out of children

PURPOSE

Nourish hair